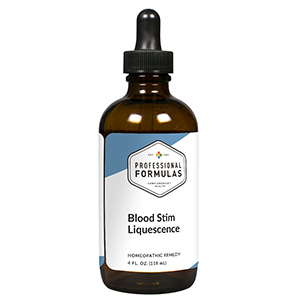 DRUG LABEL: Blood Stim Liquescence
NDC: 63083-3004 | Form: LIQUID
Manufacturer: Professional Complementary Health Formulas
Category: homeopathic | Type: HUMAN OTC DRUG LABEL
Date: 20190815

ACTIVE INGREDIENTS: ONION 1 [hp_X]/118 mL; HYSSOPUS OFFICINALIS WHOLE 1 [hp_X]/118 mL; LARREA DIVARICATA WHOLE 2 [hp_X]/118 mL; URTICA URENS WHOLE 2 [hp_X]/118 mL; MELILOTUS ALBUS TOP 3 [hp_X]/118 mL; TRIFOLIUM PRATENSE FLOWER 3 [hp_X]/118 mL; PERVINCA MINOR WHOLE 3 [hp_X]/118 mL; CAMPHOR (NATURAL) 4 [hp_X]/118 mL; CAPSICUM 5 [hp_X]/118 mL; BOS TAURUS BONE MARROW 6 [hp_X]/118 mL; FERRIC CATION 6 [hp_X]/118 mL; FERROSOFERRIC PHOSPHATE 6 [hp_X]/118 mL; ENGLISH WALNUT 6 [hp_X]/118 mL; BEEF LIVER 6 [hp_X]/118 mL; MAGNESIUM PHOSPHATE, DIBASIC TRIHYDRATE 6 [hp_X]/118 mL; BOS TAURUS PITUITARY GLAND, POSTERIOR 6 [hp_X]/118 mL; BOS TAURUS SPLEEN 6 [hp_X]/118 mL; RANCID BEEF 12 [hp_X]/118 mL
INACTIVE INGREDIENTS: ALCOHOL; WATER

T4

ACTIVE INGREDIENTS

Allium cepa 1X
Hyssopus officinalis 1X
Larrea divaricata 2X
Urtica urens 2X
Melilotus alba 3X
Trifolium pratense 3X
Vinca minor 3X
Camphora 4X
Capsicum annuum 5X
Bone marrow 6X
Ferrum muriaticum 6X
Ferrum phosphoricum 6X
Juglans regia 6X
Liver 6X
Magnesia phosphorica 6X
Pituitary 6X
Spleen 6X
Pyrogenium 12X

QUESTIONS

Professional Formulas

PO Box 2034 Lake Oswego, OR 97035

INDICATIONS

For the temporary relief of fatigue, weakness, exhaustion, flushed skin, muscle twitches, shortness of breath, trouble concentrating, occasional headache, or feelings of discomfort or uneasiness.*

PURPOSE

*Claims based on traditional homeopathic practice, not accepted medical evidence. Not FDA evaluated.

WARNINGS

Consult a doctor if condition worsens or if symptoms persist. Keep out of the reach of children. In case of overdose, get medical help or contact a poison control center right away. If pregnant or breastfeeding, ask a healthcare professional before use.

Keep out of the reach of children.

PREGNANCY OR BREAST FEEDING

If pregnant or breastfeeding, ask a healthcare professional before use.

DIRECTIONS

Place drops under tongue 30 minutes before/after meals. Adults and children 12 years and over: Take one full dropper up to 2 times per day. Consult a physician for use in children under 12 years of age.

OTHER INFORMATION

Tamper resistant. If seal is broken, do not use. After opening, close container tightly and store at room temperature away from heat.

INACTIVE INGREDIENTS

20% ethanol, purified water.

LABEL

Est 1985

Professional Formulas

Complementary Health

Blood Stim Liquescence

Homeopathic Remedy

4 FL. OZ. (118 mL)